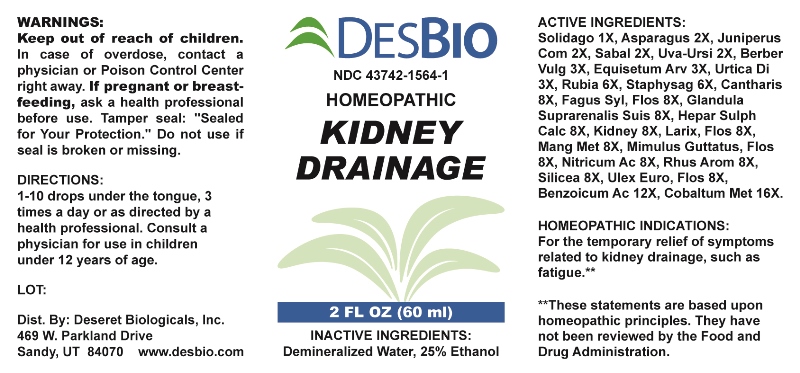 DRUG LABEL: Kidney Drainage
NDC: 43742-1564 | Form: LIQUID
Manufacturer: Deseret Biologicals, Inc.
Category: homeopathic | Type: HUMAN PRESCRIPTION DRUG LABEL
Date: 20230627

ACTIVE INGREDIENTS: SOLIDAGO VIRGAUREA FLOWERING TOP 1 [hp_X]/1 mL; ASPARAGUS 2 [hp_X]/1 mL; JUNIPERUS COMMUNIS WHOLE 2 [hp_X]/1 mL; SAW PALMETTO 2 [hp_X]/1 mL; ARCTOSTAPHYLOS UVA-URSI LEAF 2 [hp_X]/1 mL; BERBERIS VULGARIS ROOT BARK 3 [hp_X]/1 mL; EQUISETUM ARVENSE TOP 3 [hp_X]/1 mL; URTICA DIOICA 3 [hp_X]/1 mL; RUBIA TINCTORUM ROOT 6 [hp_X]/1 mL; DELPHINIUM STAPHISAGRIA SEED 6 [hp_X]/1 mL; LYTTA VESICATORIA 8 [hp_X]/1 mL; FAGUS SYLVATICA FLOWERING TOP 8 [hp_X]/1 mL; SUS SCROFA ADRENAL GLAND 8 [hp_X]/1 mL; CALCIUM SULFIDE 8 [hp_X]/1 mL; PORK KIDNEY 8 [hp_X]/1 mL; LARIX DECIDUA FLOWERING TOP 8 [hp_X]/1 mL; MANGANESE 8 [hp_X]/1 mL; MIMULUS GUTTATUS FLOWERING TOP 8 [hp_X]/1 mL; NITRIC ACID 8 [hp_X]/1 mL; RHUS AROMATICA ROOT BARK 8 [hp_X]/1 mL; SILICON DIOXIDE 8 [hp_X]/1 mL; ULEX EUROPAEUS FLOWER 8 [hp_X]/1 mL; BENZOIC ACID 12 [hp_X]/1 mL; COBALT 16 [hp_X]/1 mL
INACTIVE INGREDIENTS: WATER; ALCOHOL

DRUG FACTS:

ACTIVE INGREDIENTS:

Solidago Virgaurea 1X, Asparagus Officinalis 2X, Juniperus Communis 2X, Sabal Serrulata 2X, Uva-Ursi 2X, Berberis Vulgaris 3X, Equisetum Arvense 3X, Urtica Dioica 3X, Rubia Tinctorum 6X, Staphysagria 6X, Cantharis 8X, Fagus Sylvatica, Flos 8X, Glandula Suprarenalis Suis 8X, Hepar Sulphuris Calcareum 8X, Kidney (Suis) 8X, Larix Decidua, Flos 8X, Manganum Metallicum 8X, Mimulus Guttatus, Flos 8X, Nitricum Acidum 8X, Rhus Aromatica 8X, Silicea 8X, Ulex Europaeus, Flos 8X, Benzoicum Acidum 12X, Cobaltum Metallicum 16X

HOMEOPATHIC INDICATIONS:

For the temporary relief of symptoms related to kidney drainage, such as fatigue.**

**These statements are based upon traditional homeopathic practice. They have not been reviewed by the Food and Drug Administration.

WARNINGS:

Keep out of reach of children. In case of overdose, contact a physician or Poison Control Center right away.

If pregnant or breast-feeding, ask a health professional before use.

Tamper seal: "Sealed for Your Protection." Do not use if seal is broken or missing.

Keep out of reach of children. In case of overdose, contact a physician or Poison Control Center right away.

DIRECTIONS:

1-10 drops under the tongue, 3 times a day or as directed by a health professional. Consult a physician for use in children under 12 years of age.

HOMEOPATHIC INDICATIONS:

For the temporary relief of symptoms related to kidney drainage, such as fatigue.**

**These statements are based upon traditional homeopathic practice. They have not been reviewed by the Food and Drug Administration.

INACTIVE INGREDIENTS:

Demineralized Water, 25% Ethanol

QUESTIONS:

Dist. By: Deseret Biologicals, Inc.

469 W. Parkland Drive

Sandy, UT 84070 www.desbio.com

PACKAGE DISPLAY LABEL:

DESBIO

NDC 43742-1564-1

HOMEOPATHIC

KIDNEY

DRAINAGE

2 FL OZ (60 ml)